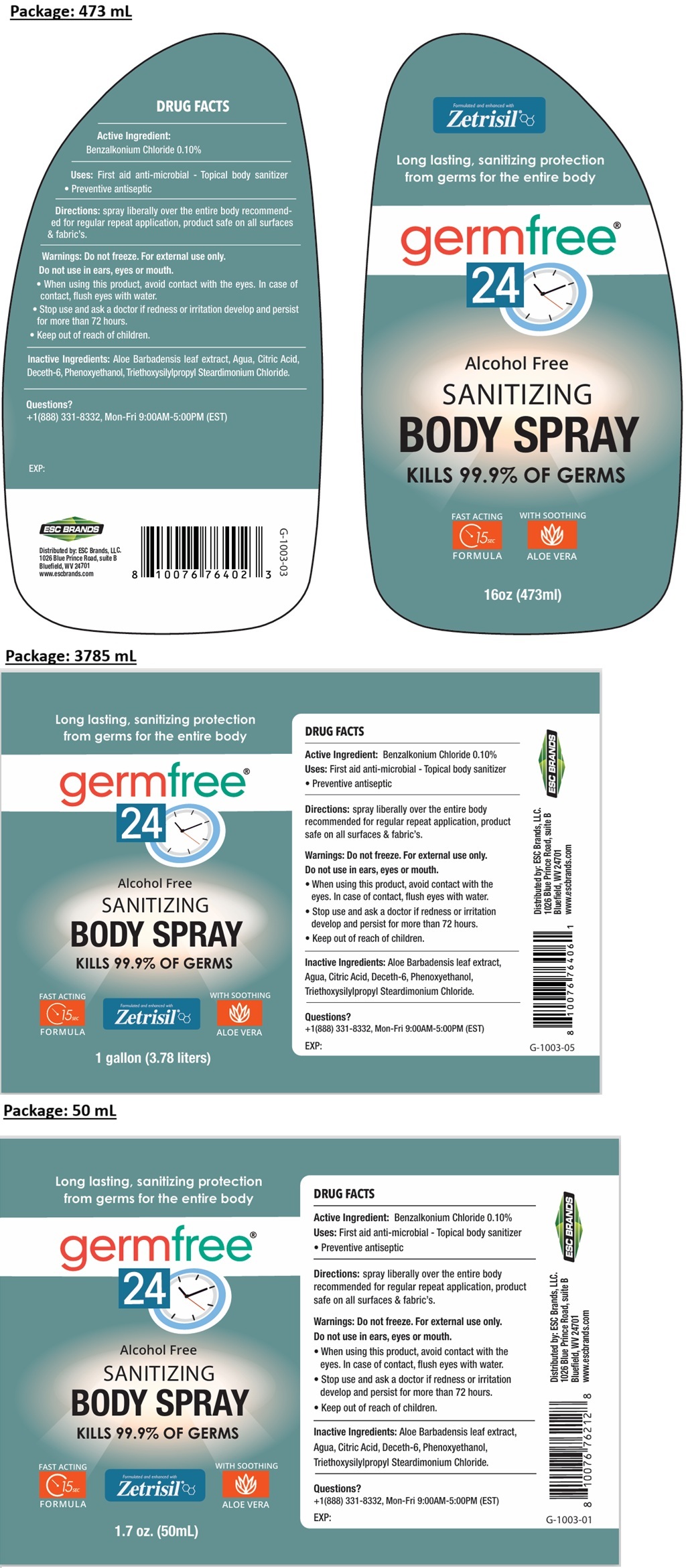 DRUG LABEL: germfree24 Sanitizing Body-Spray
NDC: 71884-017 | Form: SPRAY
Manufacturer: Enviro Specialty Chemicals Inc
Category: otc | Type: HUMAN OTC DRUG LABEL
Date: 20260129

ACTIVE INGREDIENTS: BENZALKONIUM CHLORIDE 0.10 g/100 mL
INACTIVE INGREDIENTS: ALOE VERA LEAF; WATER; CITRIC ACID MONOHYDRATE; DECETH-6; PHENOXYETHANOL; TRIETHOXYSILYLPROPYL STEARDIMONIUM CHLORIDE

germfree® 24 SANITIZING BODY SPRAY

Active Ingredient:

Benzalkonium Chloride 0.10%

Purpose

Antiseptic

Uses:

First aid anti-microbial - Topical body sanitizer • Preventive antiseptic

Directions:

spray liberally over the entire body recommended for regular repeat application, product safe on all surfaces & fabric's.

Warnings:

Do not freeze. For external use only.

Do not use in ears, eyes or mouth.

• When using this product, avoid contact with the eyes. In case of contact, flush eyes with water.

• Stop use and ask a doctor if redness or irritation develop and persist for more than 72 hours.

• Keep out of reach of children.

Inactive Ingredients:

Aloe Barbadensis leaf extract, Agua, Citric Acid, Deceth-6, Phenoxyethanol, Triethoxysilylpropyl Steardimonium Chloride.

Questions?

+1(888) 331-8332, Mon-Fri 9:00AM-5:00PM (EST)

Long lasting, sanitizing protection from germs for the entire body

Alcohol Free

KILLS 99.9% OF GERMS

FAST ACTING 15 SEC FORMULA

Formulated and enhanced with Zetrisil®

WITH SOOTHING ALOE VERA

Distributed by: ESC Brands, LLC.
1026 Blue Prince Road, suite B
Bluefield, WV 24701

www.escbrands.com